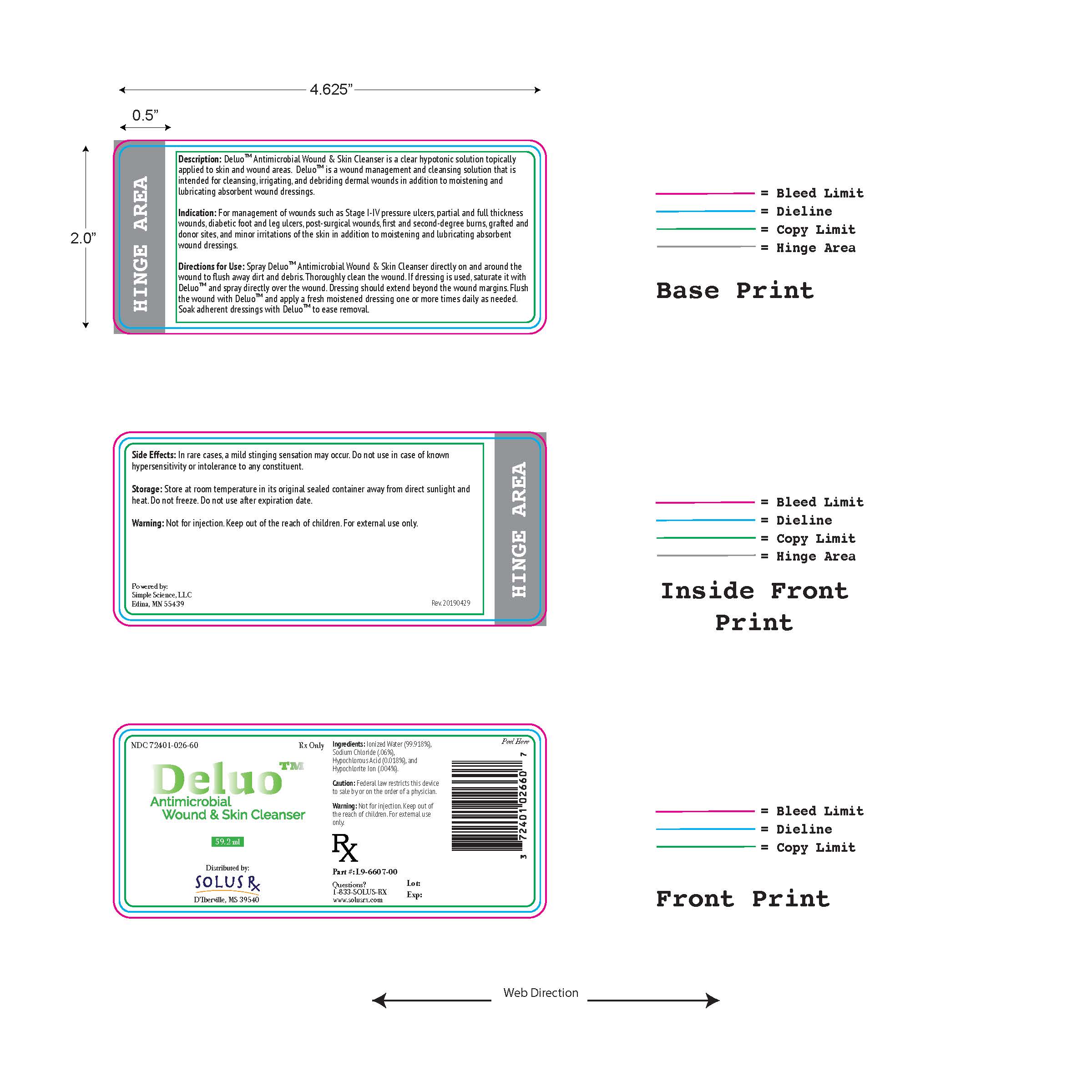 DRUG LABEL: Deluo Antimicrobial Wound and Skin Cleanser
NDC: 72401-026
Manufacturer: Solus Rx, LLC
Category: other | Type: PRESCRIPTION MEDICAL DEVICE LABEL
Date: 20190502

Deluo Antimicrobial Wound & Skin Cleanser

DESCRIPTION

Deluo™ Antimicrobial Wound & Skin Cleanser is a clear hypotonic solution topically applied to skin and wound areas. Deluo™ is a wound management and cleansing solution that is intended for cleansing, irrigating, and debriding dermal wounds in addition to moistening and lubricating absorbent wound dressings.

INDICATIONS

Deluo™ Antimicrobial Wound & Skin Cleanser is indicated for management of wounds such as Stage I-IV pressure ulcers, partial and full thickness wounds, diabetic foot and leg ulcers, post-surgical wounds, first and second-degree burns, grafted and donor sites, and minor irritations of the skin in addition to moistening and lubricating absorbent wound dressings.

SIDE EFFECTS

In rare cases, a mild stinging sensation may occur. Do not use in case of known hypersensitivity or intolerance to any constituent.

DIRECTIONS

Spray Deluo™ Antimicrobial Wound & Skin Cleanser directly on and around the wound to flush away dirt and debris. Thoroughly clean the wound. If dressing is used, saturate it with Deluo™ and spray directly over the wound. Dressing should extend beyond the wound margins. Flush the wound with Deluo™ and apply a fresh moistened dressing one or more times daily as needed. Soak adherent dressings with Deluo™ to ease removal.

WARNING

Not for injection. Keep out of the reach of children. For external use only.

STORAGE

Store at room temperature in its original sealed container away from direct sunlight and heat. Do not freeze. Do not use after expiration date.

HOW SUPPLIED

Deluo™ Antimicrobial Wound & Skin Cleanser is supplied in a 59.2mL blue spray bottle, NDC 72401-026-60.

RX ONLY.

Made in the USA.

Distributed by:

Solus Rx, LLC

D'Iberville, MS 39540